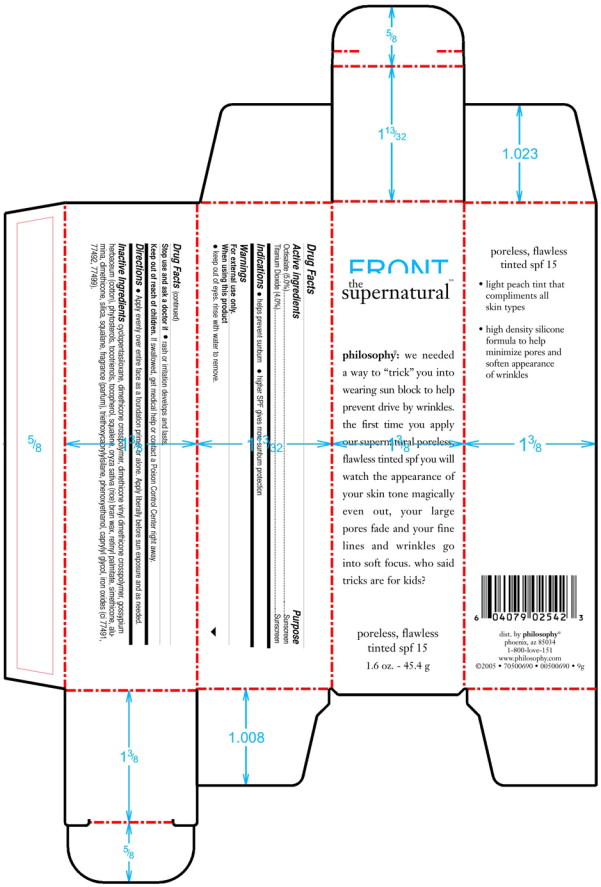 DRUG LABEL: Supernatural Poreless Flawless Tinted SPF 15
NDC: 50184-3800 | Form: CREAM
Manufacturer: Philosophy, Inc.
Category: otc | Type: HUMAN OTC DRUG LABEL
Date: 20100129

ACTIVE INGREDIENTS: Titanium Dioxide 40 mg/1 g; OCTISALATE 50 mg/1 g
INACTIVE INGREDIENTS: Cyclomethicone 5; Levant Cotton Oil; .Beta.-Sitosterol; Alpha-Tocopherol; Squalene; Rice Germ Oil; Vitamin A Palmitate; Aluminum Oxide; Dimethicone; Silicon Dioxide; Squalane; Triethoxycaprylylsilane; Phenoxyethanol; Caprylyl Glycol; Ferric Oxide Red; Ferric Oxide Yellow; Ferrosoferric Oxide

Drug Facts

Active ingredients

Octisalate 5% w/w

Titanium Dioxide 4% w/w

INACTIVE INGREDIENT

Cyclopentasiloxane 74.863% w/w

Dimethicone Crosspolymer 6.25% w/w

Dimethicone Vinyl Dimethicone crosspolymer 5.309% w/w

Grossypium Herbaceum Cotton 1.48% w/w

Phytosterols 0.037% w/w

Tocotrienols 0.0160% w/w

Tocopherol 0.0170% w/w

Squalene 0.0150% w/w

Oryza Sativa (Rice) Bran Wax 0.0150% w/w

Retinyl Palmitate 0.100% w/w

Simethicone 0.0025% w/w

Alumina 0.0025% w/w

Dimethicone 0.2400% w/w

Silica 0.400% w/w

Squalane 0.200% w/w

Fragrance 0.1000% w/w

Triethoxycaprylylsilane 0.0045% w/w

Phenoxyethanol 0.2750% w/w

Caprylyl Glycol 0.2250% w/w

Iron Oxides 0.4485% w/w

STOP USE AND ASK DOCTOR IF RASH OR IRRITATION DEVELOPS AND LASTS

GENERAL PRECAUTIONS

WARNINGS: FOR EXTERNAL USE ONLY

WHEN USING THIS PRODUCT:

KEEP OUT OF EYES. RINSE WITH WATER TO REMOVE.

KEEP OUT OF REACH OF CHILDREN.

IF SWALLOWED, GET MEDICAL HELP OR CONTACT A POISON CENTER RIGHT AWAY.

PURPOSE

INDICATIONS:

HELPS PREVENT SUNBURN

HIGHER SPF GIVES MORE SUNBURN PROTECTION

INDICATIONS:

HELPS PREVENT SUNBURN

HIGHER SPF GIVES MORE SUNBURN PROTECTION

DIRECTIONS: APPLY EVENLY OVER ENTIRE FACE AS A FOUNDATION OR PRIMER OR ALONE. APPLY LIBERALLY BEFORE SUN EXPOSURE AND AS NEEDED.